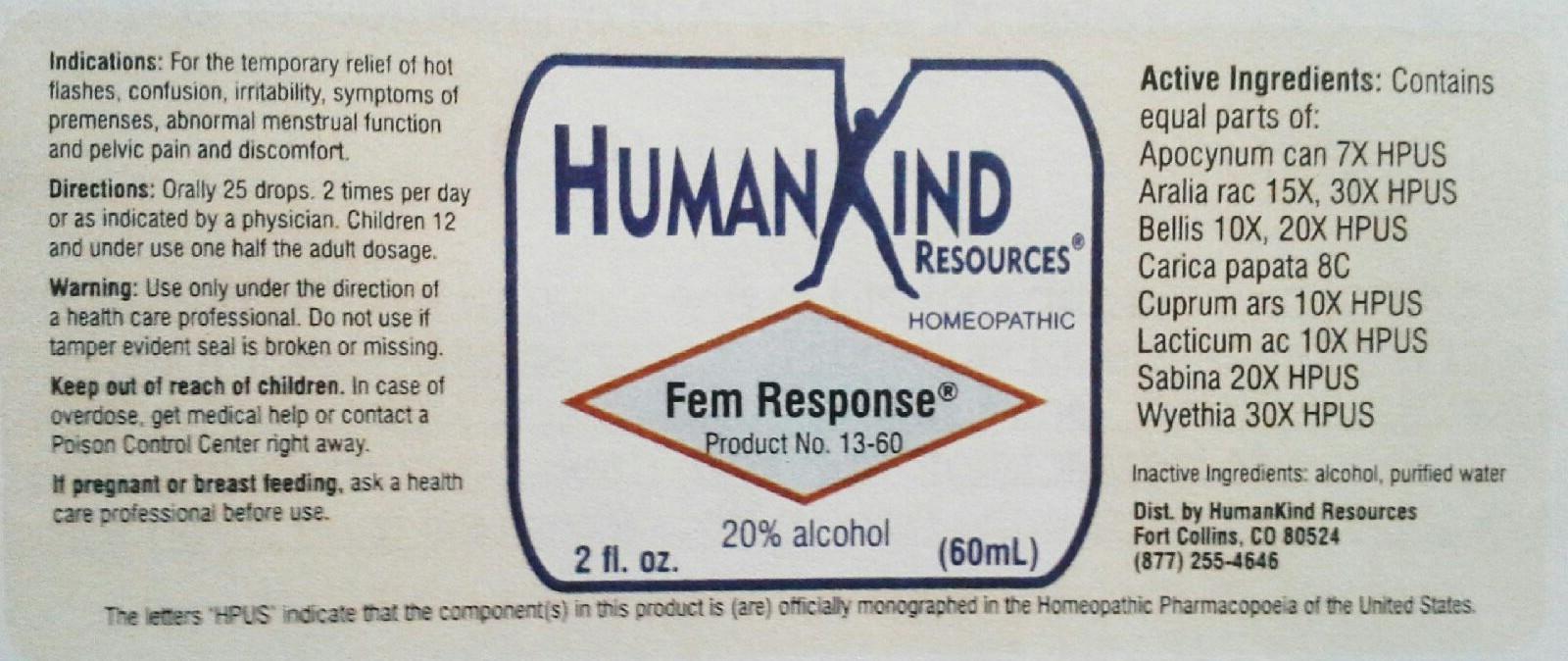 DRUG LABEL: Fem Response
NDC: 64616-091 | Form: LIQUID
Manufacturer: Vitality Works, Inc.
Category: homeopathic | Type: HUMAN OTC DRUG LABEL
Date: 20251217

ACTIVE INGREDIENTS: APOCYNUM CANNABINUM ROOT 7 [hp_X]/1 mL; ARALIA RACEMOSA ROOT 30 [hp_X]/1 mL; BELLIS PERENNIS 20 [hp_X]/1 mL; PAPAYA SEED 8 [hp_C]/1 mL; CUPRIC ARSENITE 10 [hp_X]/1 mL; LACTIC ACID, DL- 10 [hp_X]/1 mL; JUNIPERUS SABINA LEAFY TWIG 20 [hp_X]/1 mL; WYETHIA HELENIOIDES ROOT 30 [hp_X]/1 mL
INACTIVE INGREDIENTS: ALCOHOL; WATER

Fem Response

Fem Response

Apocynum Cannabinum 7X Cuprum Arsenicosum 10X

Aralia Racemosa 15X, 30X Lacticum Acidum 10X

Bellis Perennis 10X, 20X Sabina 20X

Carica Papata 8C Wyethia Heleniodes 30X

Fem Response

Alcohol, Purified Water

Fem Response

Use only under the direction of a health care professional. Do not use if tamper evident seal is broke or missing.

Fem Response

Keep out of reach of children. In case of overdose, get medical help or contact a Poison Control Center right away.

Fem Response

For the temporary relief of hot flashes, confusion, irritability, syptoms of premenses, abnormal menstrual function and pelvic pain and discomfort.

Fem Response

Orally 25 drops, 2 times per day or as indicated by a physician. Children 12 and under use one half the adult dosage.

Fem Response

Helps ease hot flashes, confusion, irritability symptoms of premenses, abnormal menstrual function and pelvic pain and discomfort.